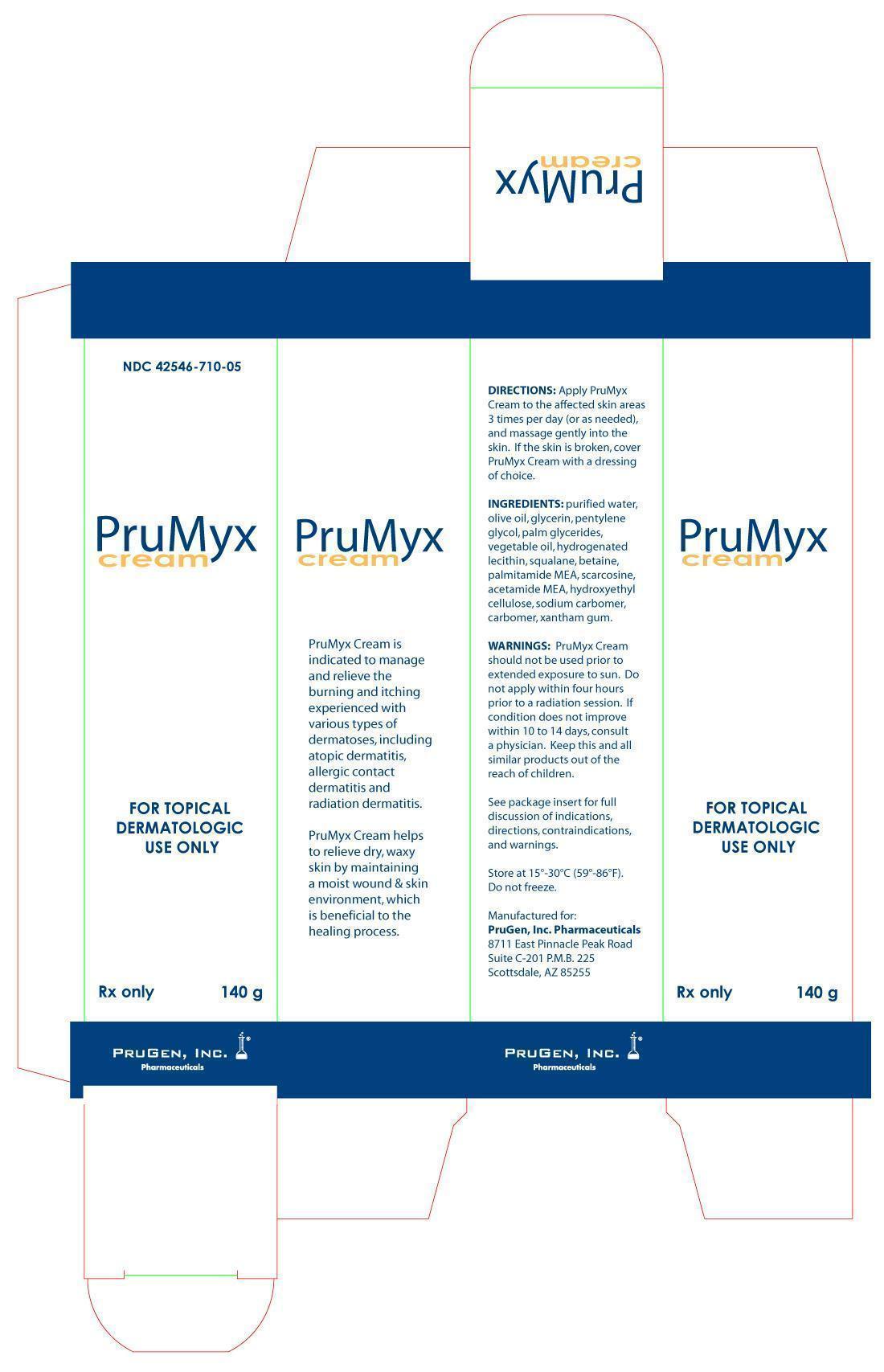 DRUG LABEL: PruMyx
NDC: 42546-710
Manufacturer: PruGen, Inc.
Category: other | Type: PRESCRIPTION MEDICAL DEVICE LABEL
Date: 20120822

PruMyx External Cream

DESCRIPTION

PruMyx Cream is a fragrance free, preservative free, water-based emulsion formulated for the management and relief of the burning and itching experienced with various types of dermatoses, including atopic dermatitis, allergic contact dermatitis and radiation dermatitis. PruMyx Cream helps to relieve the dry, waxy skin by maintaining a moist wound & skin environment, which is beneficial to the healing process.

INDICATIONS & USAGE

PruMyx Cream is indicated to manage and relieve the burning and itching experienced with various types of dermatoses, including atopic dermatitis, allergic contact dermatitis and radiation dermatitis. PruMyx Cream helps to relieve dry, waxy skin by maintaining a moist wound & skin environment, which is beneficial to the healing process.

CONTRAINDICATIONS

PruMyx Cream is contraindicated in persons with a known hypersensitivity to any of the components of the formulation.

WARNINGS

In radiation therapy, PruMyx Cream may be applied as indicated by the treating Radiation Oncologist. Do not apply 4 hours prior to a radiation session.

PRECAUTIONS AND OBSERVATIONS

- PruMyx Cream is for external use only.

- PruMyx Cream does not contain a sunscreen and should not be used prior to extended exposure to the sun.

- If clinical signs of infection are present, appropriate treatment should be initiated; use of PruMyx Cream may be continued during the anti-infective therapy.

- If the condition does not improve within 10 – 14 days, consult a physician.

- Keep this and other similar products out of the reach of children.

- PruMyx Cream may dissolve fuchsin when this dye is used to define the margins of the radiation fields to be treated.

INSTRUCTIONS FOR USE

Apply PruMyx Cream to the affected skin areas 3 times per day (or as needed), and massage gently into the skin. If the skin is broken, cover PruMyx Cream with a dressing of choice.

INGREDIENTS

PruMyx Cream contains purified water, olive oil, glycerin, pentylene glycol, palm glycerides, vegetable oil, hydrogenated lecithin, squalane, betaine, palmitamide MEA, sarcosine, acetamide MEA, hydroxyethyl cellulose, sodium carbomer, carbomer, xanthan gum.

HOW SUPPLIED

PruMyx Cream is available in a 140 gram tube, NDC 42546-710-05.

Store at 15ºC to 30ºC (59ºF to 86ºF). Do not freeze.

PruGen, Inc. Pharmaceuticals

8711 East Pinnacle Peak Road

Suite C-201 P.M.B.225

Scottsdale, AZ 85255

PruMyx Carton Label

NDC 42546-710-05

PruMyx Cream

For Topical Dermatologic Use Only

Rx Only

140g

PruGen, Inc. Pharmaceuticals